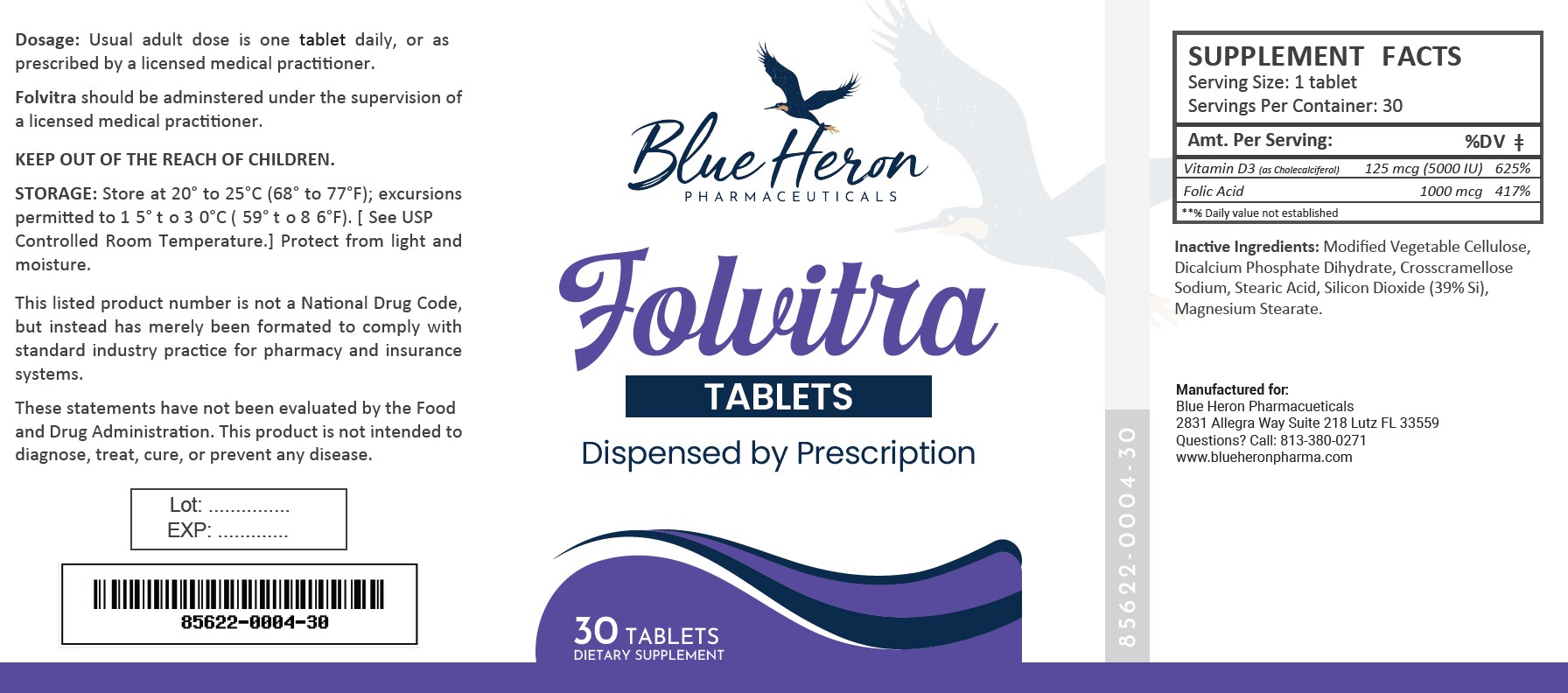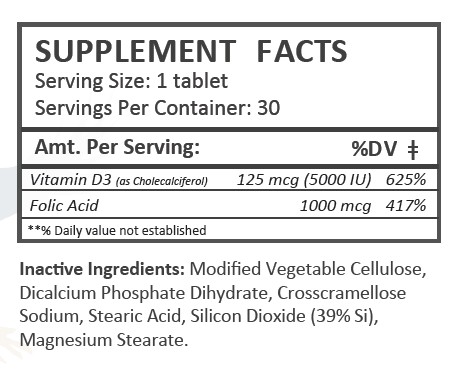 DRUG LABEL: Folvitra
NDC: 85622-004 | Form: Tablet
Manufacturer: Blue Heron Pharmaceuticals, LLC
Category: prescription | Type: HUMAN PRESCRIPTION DRUG LABEL
Date: 20251013

ACTIVE INGREDIENTS: CHOLECALCIFEROL 125 ug/1 1; FOLIC ACID 1 mg/1 1

Folvitra

HEALTH CLAIM:

Folvitra - Vitamin D3 and Folic Acid Tablets

DESCRIPTION:

Folvitra Multivitamin Capsules are clear capsules dispensed in plastic bottles of 30 ct.

85622-0004-30

Reserved for Professional Recommendation

Folvitra is an orally administered prescription folate product for the dietary management of patients with unique nutritional needs requiring increased folate levels and Vitamin D supplementation due to Vitamin D deficiency.

Folvitra Tablets should be administered under the supervision of a licensed medical practitioner.

This listed product is not a National Drug Code, but instead has merely been formatted to comply with standard industry practice for pharmacy and insurance computer systems.

These statements have not been evaluated by the Food and Drug Administration. This product is not intended to diagnose, treat, cure or prevent any disease.

All prescriptions using this product shall be pursuant to state statutes as applicable. This is not an Orange Book product. This product may be administered only under a physician’s supervision. There are no implied or explicit claims on therapeutic equivalence.

Manufactured for:

Blue Heron Pharmaceuticals

Lutz, FL 33559

WARNINGS:

This product is contraindicated in patients with a known hypersensitivity to any of the ingredients.

Folvitra Tablets should only be used under the direction and supervision of a licensed medical practitioner. Use with caution in patients that may have a medical condition, are pregnant, lactating, trying to conceive, under the age of 18, or taking medications.

These statements have not been evaluated by the Food and Drug Administration. This product is not intended to diagnose, treat, cure, or prevent any disease.

Tell your doctor if you have: kidney problems, thyroid disease. This medication should be used as directed during pregnancy or while breast-feeding. Consult your doctor about the risks and benefits.

Folic acid alone is improper therapy in the treatment of pernicious anemia and other megaloblastic anemias where vitamin B12 is deficient. Folic acid in doses above 0.1 mg daily may obscure pernicious anemia in that hematologic remission can occur while neurological manifestations progress.

DOSAGE:

Usual adult dose is 1 tablet by mouth daily once daily, or as prescribed by a licensed medical practitioner.

PRECAUTIONS:

CONTRAINDICATIONS
This product is contraindicated in patients with known hypersensitivity to any of the ingredients.

PRECAUTIONS
This product is contraindicated in patients with a known hypersensitivity to any of the ingredients.

ADVERSE REACTIONS
Allergic sensitizations have been reported following oral administration of folic acid. Consult your physician immediately if adverse side effects occur.

KEEP OUT OF THE REACH OF CHILDREN.

STORAGE:

Store at 20° to 25°C (68° to 77°F); excursions permitted to 15° to 30°C (59° to 86°F). [See USP Controlled Room Temperature.] Protect from light and moisture.